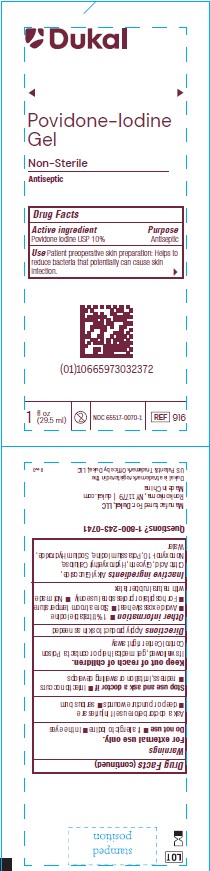 DRUG LABEL: Povidone-Iodine Gel
NDC: 65517-0070 | Form: GEL
Manufacturer: Dukal LLC
Category: otc | Type: HUMAN OTC DRUG LABEL
Date: 20251119

ACTIVE INGREDIENTS: POVIDONE-IODINE 1 g/100 mL
INACTIVE INGREDIENTS: WATER; SODIUM HYDROXIDE; HYDROXYETHYL CELLULOSE (2000 CPS AT 1%); NONOXYNOL-10; GLYCERIN; ANHYDROUS CITRIC ACID; C12-20 ALKYL GLUCOSIDE; POTASSIUM IODIDE

Active Ingredient

Povidone-Iodine USP 10%

Purpose

Antiseptic

Use

Patient preoperative skin preparation. Helps to reduce bacteria that potentially can cause skin infection.

Warnings

For External Use Only

Do not use

- if allergic to iodine
- in the eyes

Ask a doctor before use if injuries are

- deep or puncture wounds
- serious burn

Stop use and ask doctor

- infection occurs
- redness, irritation or swelling develops

Keep out of reach of children

If swallowed, get medical help or contact Poison Control Center right away

Directions

apply product to skin as needed

Other information

- 1% titratable iodine
- Avoid excessive heat
- Store at room temperature
- For hospital or professional use only
- Not made with natural rubber latex

Inactive Ingredients

Alkyl Glucoside, Citric Acid, Glycerin, Hydroxyethyl Cellulose, Nonoxynol-10, Potassium Iodide, Sodium hydroxide, Water

Principle Display Panel

Duka

Povidone-Iodine

Gel

Non-Sterile

Antispetic

Drug Facts

Active ingredient Purpose

Povidone Iodine USP 10% Antiseptic

Use Patient preoperative skin preparation. Helps to reduce bacteria

that potentially can cause skin infection.

1 fl oz (29.5ml) Do not re-use NDC-66517-0070-1 REF 916